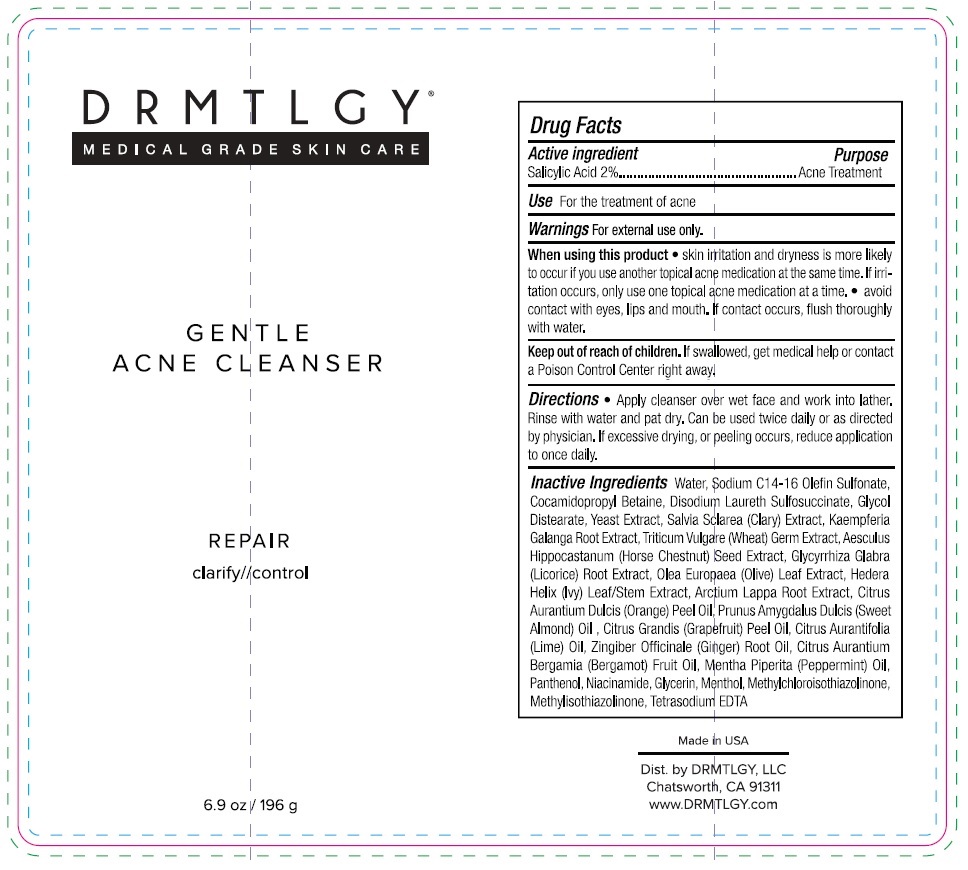 DRUG LABEL: GENTLE ACNE CLEANSER
NDC: 83286-013 | Form: LIQUID
Manufacturer: Drmtlgy, LLC
Category: otc | Type: HUMAN OTC DRUG LABEL
Date: 20250409

ACTIVE INGREDIENTS: SALICYLIC ACID 2 g/100 g
INACTIVE INGREDIENTS: WATER; SODIUM C14-16 OLEFIN SULFONATE; COCAMIDOPROPYL BETAINE; DISODIUM LAURETH SULFOSUCCINATE; GLYCOL DISTEARATE; YEAST, UNSPECIFIED; SCLAREOLIDE; KAEMPFERIA GALANGA ROOT; WHEAT GERM; HORSE CHESTNUT; GLYCYRRHIZA GLABRA (LICORICE) ROOT POWDER; OLEA EUROPAEA (OLIVE) LEAF POWDER; HEDERA HELIX TOP; ARCTIUM LAPPA ROOT; ORANGE OIL, COLD PRESSED; ALMOND OIL; CITRUS MAXIMA FRUIT RIND OIL; LIME OIL, COLD PRESSED; GINGER OIL; BERGAMOT OIL; PEPPERMINT OIL; PANTHENOL; NIACINAMIDE; GLYCERIN; MENTHOL, UNSPECIFIED FORM; METHYLCHLOROISOTHIAZOLINONE; METHYLISOTHIAZOLINONE; EDETATE SODIUM

DRMTLGY® GENTLE ACNE CLEANSER

Active ingredient

Salicylic Acid 2%

Purpose

Acne Treatment

Use

For the treatment of acne

Warnings

For external use only.

When using this product • skin irritation and dryness is more likely to occur if you use another topical acne medication at the same time. If irritation occurs, only use one topical acne medication at a time. • avoid contact with eyes, lips and mouth. If contact occurs, flush thoroughly with water.

Keep out of reach of children. If swallowed, get medical help or contact a Poison Control Center right away.

Directions

• Apply cleanser over wet face and work into lather. Rinse with water and pat dry. Can be used twice daily or as directed by physician. If excessive drying, or peeling occurs, reduce application to once daily.

Inactive Ingredients

Water, Sodium C14-16 Olefin Sulfonate, Cocamidopropyl Betaine, Disodium Laureth Sulfosuccinate, Glycol Distearate, Yeast Extract, Salvia Sclarea (Clary) Extract, Kaempferia Galanga Root Extract, Triticum Vulgare (Wheat) Germ Extract, Aesculus Hippocastanum (Horse Chestnut) Seed Extract, Glycyrrhiza Glabra (Licorice) Root Extract, Olea Europaea (Olive) Leaf Extract, Hedera Helix (Ivy) Leaf/Stem Extract, Arctium Lappa Root Extract, Citrus Aurantium Dulcis (Orange) Peel Oil, Prunus Amygdalus Dulcis (Sweet Almond) Oil, Citrus Grandis (Grapefruit) Peel Oil, Citrus Aurantifolia (Lime) Oil, Zingiber Officinale (Ginger) Root Oil, Citrus Aurantium Bergamia (Bergamot) Fruit Oil, Mentha Piperita (Peppermint) Oil, Panthenol, Niacinamide, Glycerin, Menthol, Methylchloroisothiazolinone, Methylisothiazolinone, Tetrasodium EDTA

MEDICAL GRADE SKIN CARE

REPAIR

clarify//control

Made in USA

Dist. by DRMTLGY, LLC
Chatsworth, CA 91311
www.DRMTLGY.com